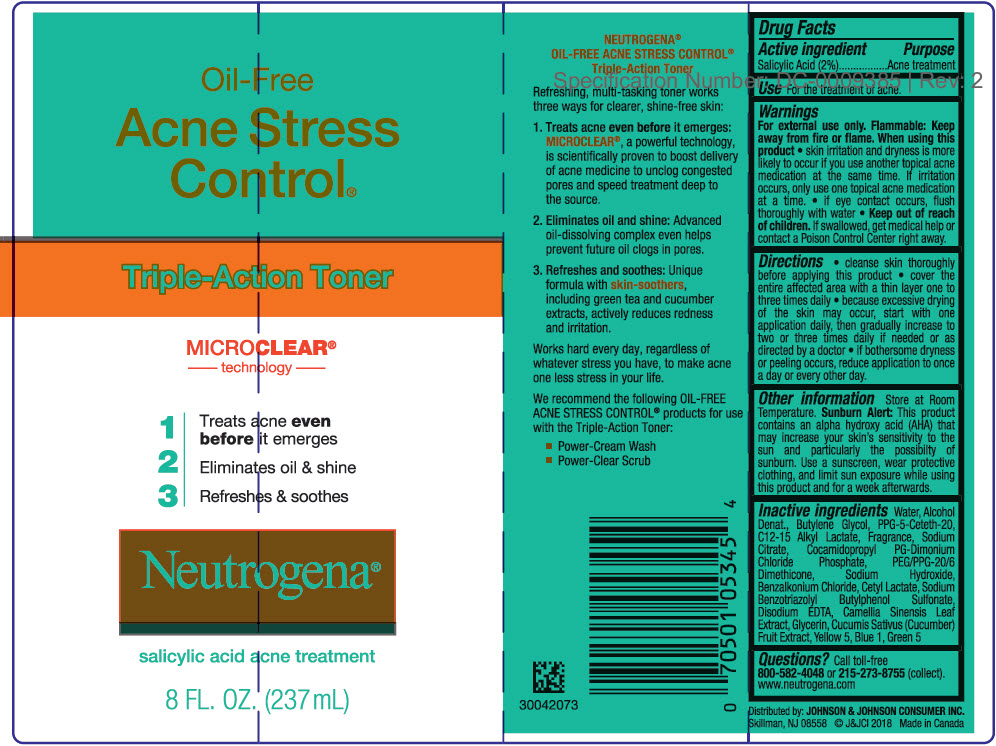 DRUG LABEL: Neutrogena Oil Free Acne Stress Control Triple Action Toner
NDC: 69968-0521 | Form: LIQUID
Manufacturer: Kenvue Brands LLC
Category: otc | Type: HUMAN OTC DRUG LABEL
Date: 20241101

ACTIVE INGREDIENTS: SALICYLIC ACID 20 mg/1 mL
INACTIVE INGREDIENTS: WATER; ALCOHOL; BUTYLENE GLYCOL; PPG-5-CETETH-20; C12-15 ALKYL LACTATE; SODIUM CITRATE, UNSPECIFIED FORM; COCAMIDOPROPYL PROPYLENE GLYCOL-DIMONIUM CHLORIDE PHOSPHATE; PEG/PPG-20/6 DIMETHICONE; SODIUM HYDROXIDE; BENZALKONIUM CHLORIDE; CETYL LACTATE; SODIUM BENZOTRIAZOLYL BUTYLPHENOL SULFONATE; EDETATE DISODIUM ANHYDROUS; GREEN TEA LEAF; GLYCERIN; CUCUMBER; FD&C YELLOW NO. 5; FD&C BLUE NO. 1; D&C GREEN NO. 5

Neutrogena® Oil - Free Acne Stress Control® Triple - Action Toner

Drug Facts

Active ingredient

Salicylic Acid (2%)

Purpose

Acne medication

Use

For the treatment of acne.

Warnings

For external use only.

Flammable: Keep away from fire or flame.

When using this product

- skin irritation and dryness is more likely to occur if you use another topical acne medication at the same time. If irritation occurs, only use one topical acne medication at a time.
- if eye contact occurs, flush thoroughly with water

- Keep out of reach of children. If swallowed, get medical help or contact a Poison Control Center right away.

Directions

- cleanse skin thoroughly before applying this product
- cover the entire affected area with a thin layer one to three times daily
- because excessive drying of the skin may occur, start with one application daily, then gradually increase to two or three times daily if needed or as directed by a doctor
- if bothersome dryness or peeling occurs, reduce application to once a day or every other day.

Other information

Store at Room Temperature.

Sunburn Alert

This product contains an alpha hydroxy acid (AHA) that may increase your skin's sensitivity to the sun and particularly the possibility of sunburn. Use a sunscreen, wear protective clothing, and limit sun exposure while using this product and for a week afterwards.

Inactive ingredients

Water, Alcohol Denat., Butylene Glycol, PPG-5-Ceteth-20, C12-15 Alkyl Lactate, Fragrance, Sodium Citrate, Cocamidopropyl PG-Dimonium Chloride Phosphate, PEG/PPG-20/6 Dimethicone, Sodium Hydroxide, Benzalkonium Chloride, Cetyl Lactate, Sodium Benzotriazolyl Butylphenol Sulfonate, Disodium EDTA, Camellia Sinensis Leaf Extract, Glycerin, Cucumis Sativus (Cucumber) Fruit Extract, Yellow 5, Blue 1, Green 5

Questions?

Call toll-free 800-582-4048 or 215-273-8755 (collect). www.neutrogena.com

Distributed by: JOHNSON & JOHNSON CONSUMER INC.
Skillman, NJ 08558

PRINCIPAL DISPLAY PANEL - 237 mL Bottle Label

Oil-Free
Acne Stress
Control®

Triple-Action Toner

MICRO CLEAR®
technology

- Treats acne even
  before it emerges
- Eliminates oil & shine
- Refreshes & soothes

Neutrogena®
salicylic acid acne treatment
8 FL. OZ. (237mL)